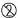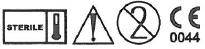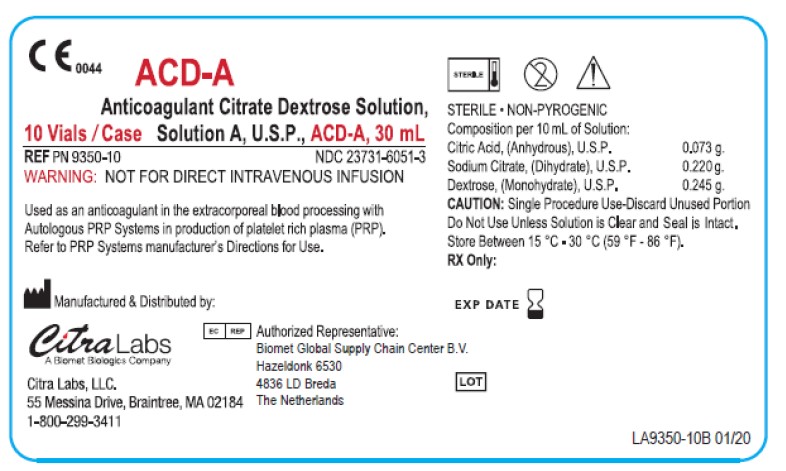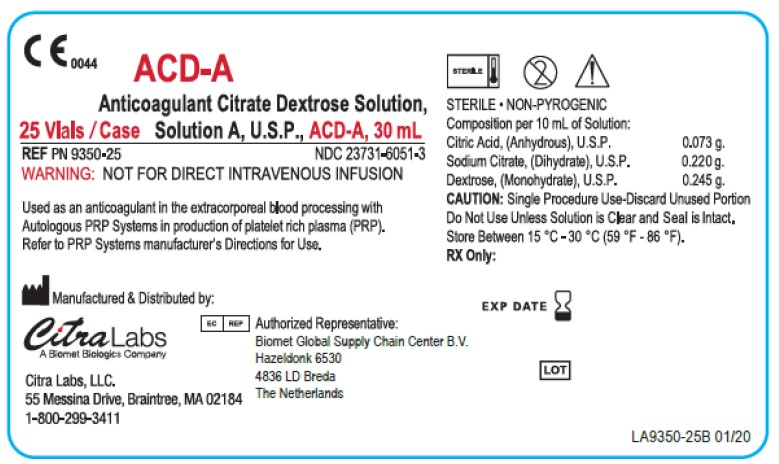 DRUG LABEL: Anticoagulant Citrate Dextrose A
NDC: 23731-6051 | Form: SOLUTION
Manufacturer: Citra Labs LLC
Category: prescription | Type: HUMAN PRESCRIPTION DRUG LABEL
Date: 20230214

ACTIVE INGREDIENTS: DEXTROSE MONOHYDRATE 0.245 g/10 mL; ANHYDROUS CITRIC ACID 0.073 g/10 mL; TRISODIUM CITRATE DIHYDRATE 0.22 g/10 mL

ACD-A
Anticoagulant Citrate Dextrose Solution,
Solution A, U.S.P., PN 9350, 30 mL
NDC 23731-6051-3

Description

Anticoagulant Citrate Dextrose Solution, Solution A, U.S.P., (ACD-A), is a sterile, non-pyrogenic solution of citric acid, sodium citrate, and dextrose, in water for injection. Each 10 mL of solution contains:

Citric Acid, anhydrous, USP | 0.073 g
Sodium Citrate, dihydrate, USP | 0.220 g
Dextrose, monohydrate, USP | 0.245 g
Water for Injection, USP | q.s.
pH: 4.5 – 5.5

Single patient use only, on a single occasion.

Clinical Pharmacology

ACD-A acts as an anticoagulant by the action of the citrate ion chelating free ionized calcium, thus making calcium unavailable to the coagulation system.

Indications and Usage

Anticoagulant Citrate Dextrose Solution, Solution A, U.S.P. (ACD-A), is intended for use as an anticoagulant in the extracorporeal blood processing with Autologous PRP Systems in production of platelet rich plasma (PRP). Refer to the manufacturer's Operator's Manual of the Autologous PRP System for the Directions for Use.

Contraindications

NOT FOR DIRECT INTRAVENOUS INFUSION

Warnings

NOT FOR DIRECT INTRAVENOUS INFUSION

Precautions

General

- Aseptic technique must be maintained at all times.
- ACD-A solution is a clear and colorless solution. If the product shows any cloudiness or turbidity, the product should be discarded.
- The closure system provides a biological barrier and should be intact – discard product if system is compromised.

Information for Patients

None.

Carcinogenesis, mutagenesis, impairment of fertility

Long-term studies in animals have not been performed to evaluate the carcinogenic potential of ACD-A.

Pregnancy

Long-term studies in animals have not been performed to evaluate the effects of ACD- A on pregnant women.

Pediatric Use

The safety and effectiveness of ACD-A in children have not been established.

Adverse Reactions

Not applicable. This product is used as an anticoagulant in the extracorporeal blood processing with Autologous PRP Systems in production of platelet rich plasma (PRP).

Overdosage

Not applicable. This product is used as an anticoagulant in the extracorporeal blood processing with Autologous PRP systems in production of platelet rich plasma (PRP).

Dosage and Administration

Refer to the manufacturer's Operator's Manual of the Autologous PRP System for the Directions for Use.

Rx Only

Caution: Federal Law (US) restricts this devise to sale by or on the order of a Physician.

How Supplied

Anticoagulant Citrate Dextrose Solution, Solution A, U.S.P., (ACD-A)

 | REF | SIZE | CASE
 | PN 9350-10 | 30 mL | 10 Vials/Case
 | PN 9350-25 | 30 mL | 25 Vials/Case

STORAGE AND HANDLING

It is recommended that the product be stored at ambient room temperature, 24 °C (75 °F); however, the product can be stored between 15 °C (59 °F) and 30 °C (86 °F). Protect from freezing and exposure to excessive heat should be minimized.

Manufactured & Distributed by:
CitraLabs™
55 Messina Drive, Braintree, MA 02184
Phone Number: 1-800-299-3411

Authorized Representative:
Biomet Global Supply Chain Center B.V.
Hazeldonk 6530
4836 LD Breda
The Netherlands

PRINCIPAL DISPLAY PANEL - 10 Vial Case Label

C E 0044

ACD-A
Anticoagulant Citrate Dextrose Solution,
10 Vials / Case Solution A, U.S.P., ACD-A, 30 mL

REF PN 9350-10
WARNING: NOT FOR DIRECT INTRAVENOUS INFUSION

Used as an anticoagulant in the extracorporeal blood processing with
Autologous PRP Systems in production of platelet rich plasma (PRP).
Refer to PRP Systems manufacturer's Directions for Use.

Manufactured & Distributed by:

CitraLabs
A Biomet Inc. Company.

Citra Labs, LLC.
55 Messina Drive, Braintree, MA 02184
1-800-299-3411

EC REP
Authorized Representative:
Biomet Global Supply Chain Center B.V.
Hazeldonk 6530
4836 LD Breda
The Netherlands

STERILE • NON-PYROGENIC
Composition per 10 mL of Solution:
Citric Acid, (Anhydrous), U.S.P. 0.073 g.
Sodium Citrate, (Dihydrate), U.S.P. 0.220 g.
Dextrose, (Monohydrate), U.S.P. 0.245 g.
CAUTION: Single Procedure Use-Discard Unused Portion
Do Not Use Unless Solution is Clear and Seal is Intact.
Store Between 15 °C - 30 °C (59 °F - 86 °F).
RX Only:

EXP DATE

LOT

LA9350-10B 01/20

PRINCIPAL DISPLAY PANEL - 25 Vial Case Label

C E 0044

ACD-A
Anticoagulant Citrate Dextrose Solution,
25 Vials / Case Solution A, U.S.P., ACD-A, 30 mL

REF PN 9350-25
WARNING: NOT FOR DIRECT INTRAVENOUS INFUSION

Used as an anticoagulant in the extracorporeal blood processing with
Autologous PRP Systems in production of platelet rich plasma (PRP).
Refer to PRP Systems manufacturer's Directions for Use.

Manufactured & Distributed by:

CitraLabs
A Biomet Inc. Company.

Citra Labs, LLC.
55 Messina Drive, Braintree, MA 02184
1-800-299-3411

EC REP
Authorized Representative:
Biomet Global Supply Chain Center B.V.
Hazeldonk 6530
4836 LD Breda
The Netherlands

STERILE • NON-PYROGENIC
Composition per 10 mL of Solution:
Citric Acid, (Anhydrous), U.S.P. 0.073 g.
Sodium Citrate, (Dihydrate), U.S.P. 0.220 g.
Dextrose, (Monohydrate), U.S.P. 0.245 g.
CAUTION: Single Procedure Use-Discard Unused Portion
Do Not Use Unless Solution is Clear and Seal is Intact.
Store Between 15 °C - 30 °C (59 °F - 86 °F).
RX Only:

EXP DATE

LOT

LA9350-25 01/20